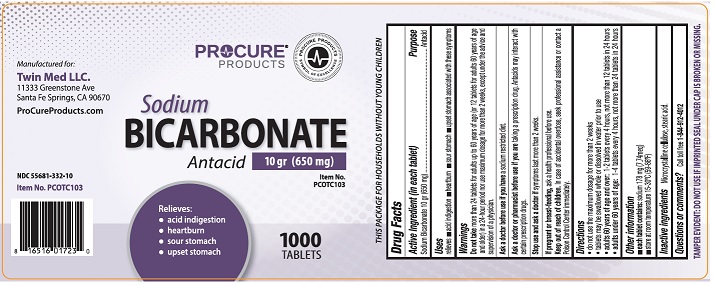 DRUG LABEL: Sodium Bicarbonate
NDC: 55681-332 | Form: TABLET
Manufacturer: TWIN MED LLC
Category: otc | Type: HUMAN OTC DRUG LABEL
Date: 20250401

ACTIVE INGREDIENTS: SODIUM BICARBONATE 650 mg/1 1
INACTIVE INGREDIENTS: STEARIC ACID; MICROCRYSTALLINE CELLULOSE

Drug Facts

Active ingredient (in each tablet)

Sodium Bicarbonate 10 gr (650 mg)

Purpose

Antacid

Uses

relieves

- acid indigestion
- heartburn
- sour stomach
- upset stomach associated with these symptoms

Warnings

DO NOT USE

Do not take more than 24 tablets for adults up to 60 years of age (or 12 tablets for adults 60 years of age and older) in a 24 hour period nor use maximum dosage for more than 2 weeks, except under the advice and supervision of a physician.

Ask a doctor before use if you have

a sodium restricted diet.

Ask a doctor or pharmacist before use if you are taking a prescription drug. Antacids may interact with certain prescription drugs.

Stop use and ask a doctor if

symptoms last more than 2 weeks.

If Pregnant or breast -feeding,

ask a health professional before use.

Keep out of reach of children.

In case of accidental overdose, seek professional assistance or contact a Poison Control Center immediately.

Directions

- do not use the maximum dosage for more than 2 weeks
- tablets may be swallowed whole or dissolved in water prior to use
- adults 60 years of age and over: 1-2 tablets every 4 hours, not more than 12 tablets in 24 hours
- adults under 60 years of age: 1-4 tablets every 4 hours, not more than 24 tablets in 24 hours

Other information

- each tablet contains:sodium 178 mg (7.74 meq)
- store at room temperature 15-30ºC (59-86°F)

Inactive ingredients

Microcrystalline cellulose, stearic acid

Questions or comments?

Call toll free 1-844-912-4012